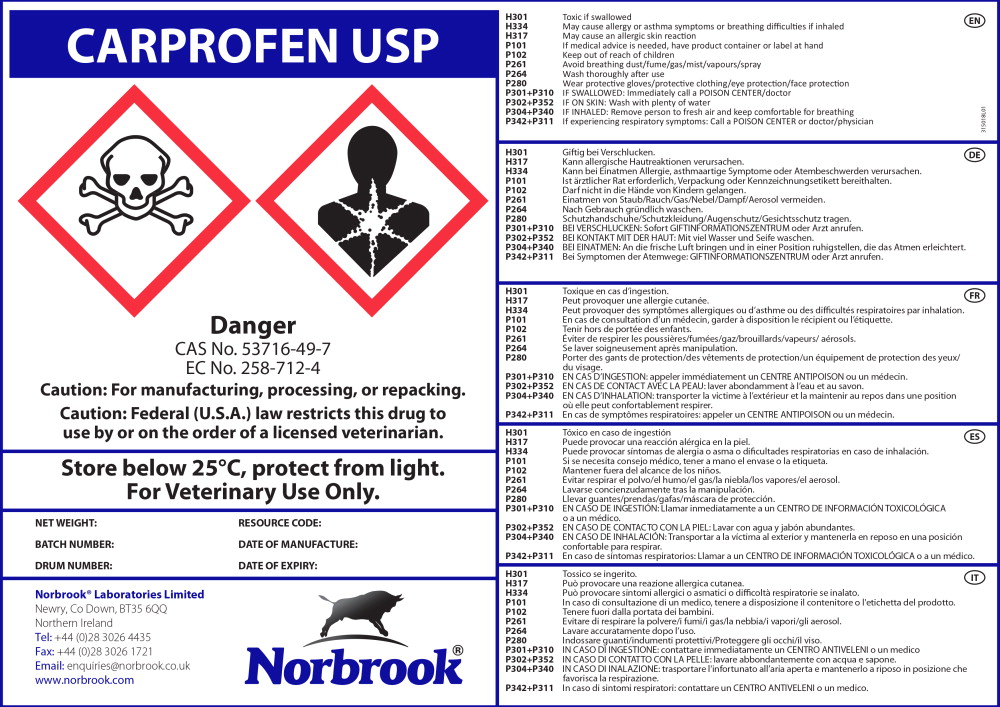 DRUG LABEL: Carprofen
NDC: 55529-620 | Form: POWDER
Manufacturer: Norbrook Laboratories Limited
Category: other | Type: BULK INGREDIENT - ANIMAL DRUG
Date: 20170515

ACTIVE INGREDIENTS: Carprofen 1 kg/1 kg

Principal Display Panel - Drum Label

CARPROFEN USP

Danger

CAS No. 53716-49-7

EC No. 258-712-4

Caution: For manufacturing, processing, or repacking.

Caution: Federal (U.S.A.) law restricts this drug to
use by or on the order of a licensed veterinarian.

Store below 25°C, protect from light.

For Veterinary Use Only.

NET WEIGHT: RESOURCE CODE:

BATCH NUMBER: DATE OF MANUFACTURE:

DRUM NUMBER: DATE OF EXPIRY:

Norbrook® Laboratories Limited

Newry, Co Down, BT35 6QQ

Northern Ireland

Tel: +44 (0)28 3026 4435

Fax: +44 (0)28 3026 1721

Email: enquiries@norbrook.co.uk

www.norbrook.com

Norbrook®